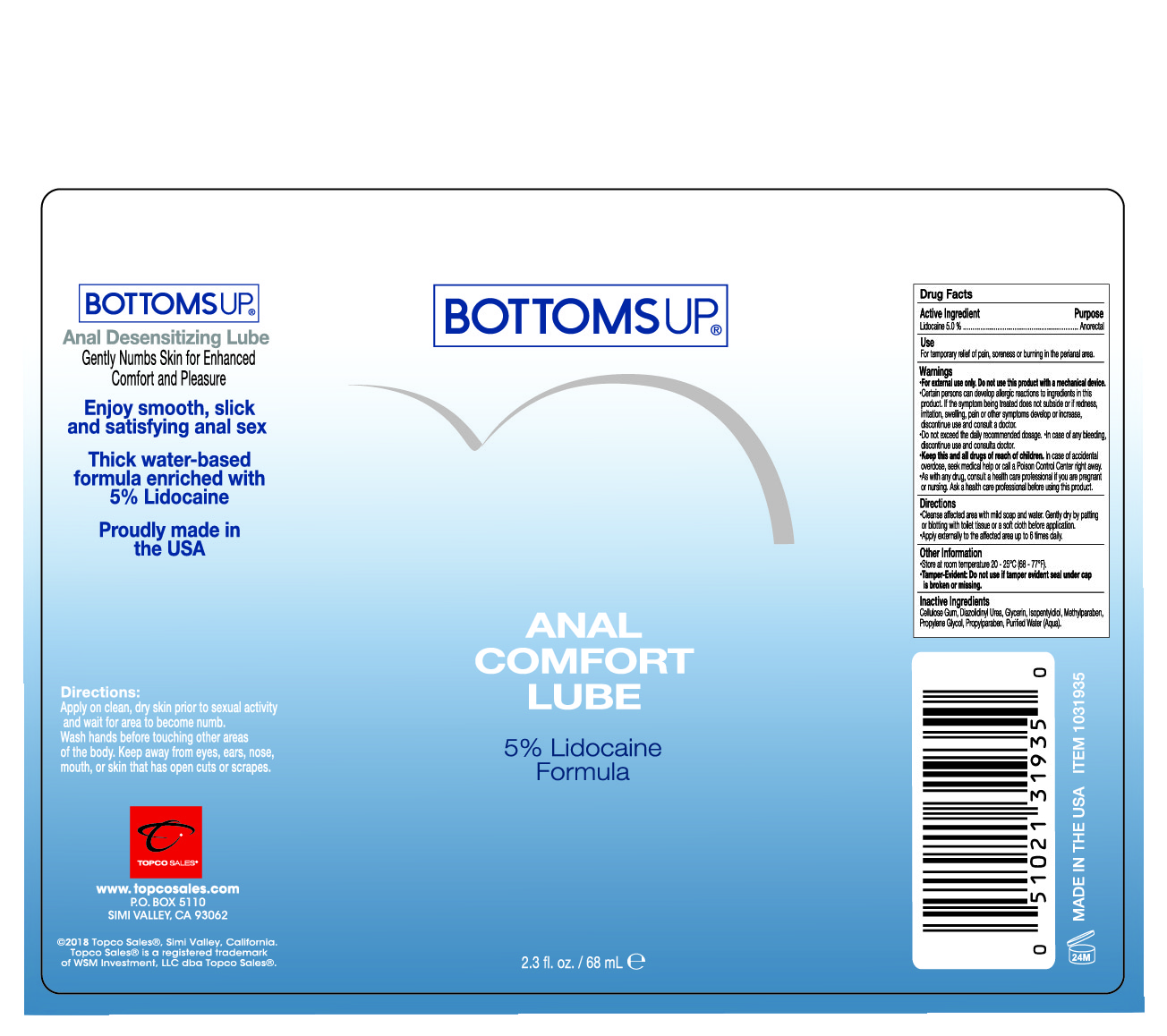 DRUG LABEL: Bottoms Up
NDC: 69797-103 | Form: LIQUID
Manufacturer: WSM Investment LLC dba Topco Sales
Category: otc | Type: HUMAN OTC DRUG LABEL
Date: 20171215

ACTIVE INGREDIENTS: LIDOCAINE 3.4 g/68 mL
INACTIVE INGREDIENTS: PROPYLENE GLYCOL; ISOPENTYLDIOL; CARBOXYMETHYLCELLULOSE CALCIUM; DIAZOLIDINYL UREA; METHYLPARABEN; WATER; PROPYLPARABEN; GLYCERIN

ACTIVE INGREDIENT

Lidocaine 5%

PURPOSE

Anorectal

INDICATIONS AND USAGE

For temporary relief of pain, soreness, or burning in the perianal area.

WARNINGS

- For external use only. Do not use this product with a mechanical device.
- Certain persons can develop allergic reactions to ingredients in this product.

If the symptom being treated does not subside or if redness, irritation, swelling, pain or other symptoms develop or increase, discontinue use and consult a doctor.

- Do not exceed the daily recommended dosage
- In case of any bleeding, discontinue use and consult a doctor.
- Avoid contact with eyes, in case of eye contact, flush with water.

KEEP OUT OF REACH OF CHILDREN

- Keep this and all drugs out of reach of children. If swallowed, seek medical help or call a Poison Control Center right away.
- As with any drug, consult a health care professional if you are pregnant or nursing. Ask a health care professional before using this product.

DOSAGE AND ADMINISTRATION

- Cleanse affected area with mild soap and water.
- Gently dry by patting or blotting with soft cloth or tissue before application.
- Apply externally to the affected area up to 6 times daily.

OTHER SAFETY INFORMATION

- Store at room temperature 20-25°C (68-77°F).
- Tamper-Evident: Do not use if tamper evident seal under cap is broken or missing.

INACTIVE INGREDIENT

Cellulose Gum, Diazolidinyl Urea, Glycerin, Isopentyldiol, Methylparaben, Propylene Glycol, Propylparaben, Purified Water (Aqua).